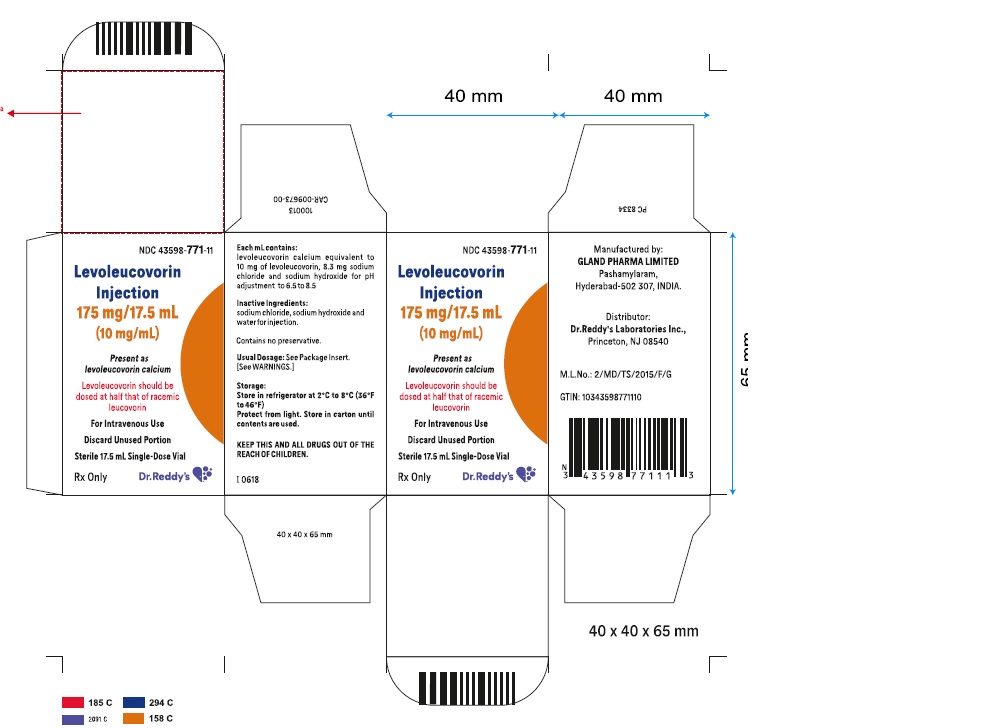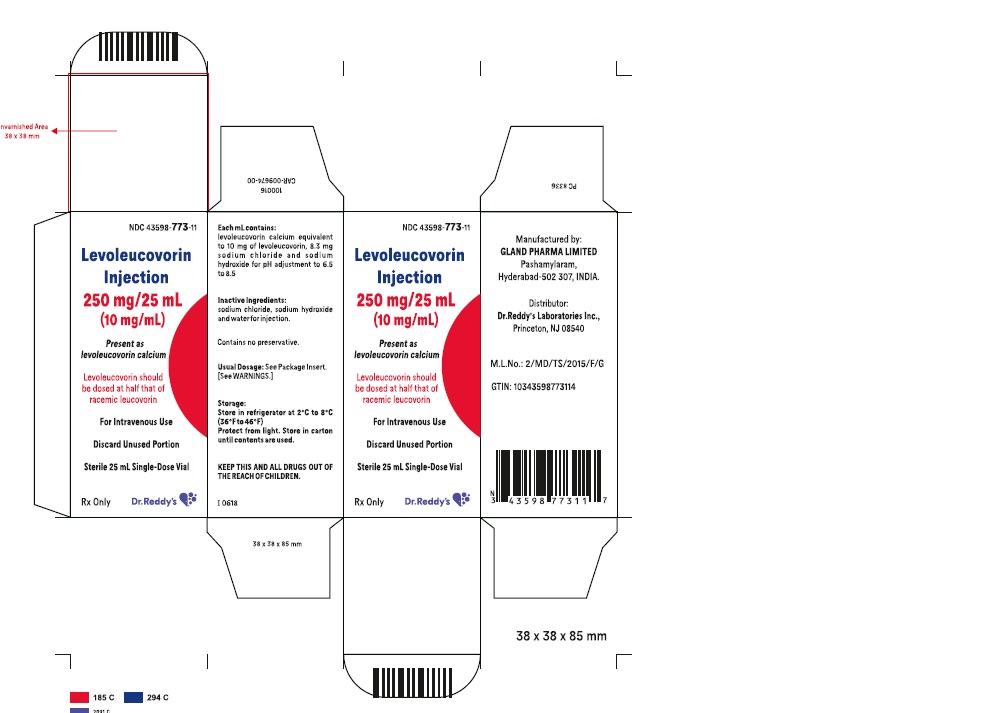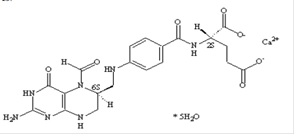 DRUG LABEL: LEVOLEUCOVORIN
NDC: 43598-771 | Form: INJECTION, SOLUTION
Manufacturer: Dr.Reddy's Laboratories Inc
Category: prescription | Type: HUMAN PRESCRIPTION DRUG LABEL
Date: 20171231

ACTIVE INGREDIENTS: Levoleucovorin Calcium 175 mg/17.5 mL
INACTIVE INGREDIENTS: Sodium Hydroxide; Sodium Chloride; Water

HIGHLIGHTS OF PRESCRIBING INFORMATION

These highlights do not include all the information needed to use LEVOLEUCOVORIN INJECTION safely and effectively.
See full prescribing information for LEVOLEUCOVORIN INJECTION.
LEVOLEUCOVORIN injection, solution for intravenous use
Initial U.S. Approval: 1952 (d,l-leucovorin), 2008 (levoleucovorin)

1 INDICATIONS AND USAGE

Levoleucovor injection is a folate analog indicated for:
· Rescue after high-dose methotrexate therapy in osteosarcoma.
· Diminishing the toxicity and counteracting the effects of impaired methotrexate elimination and of inadvertent overdosage of folic acid antagonists.
· Use in combination chemotherapy with 5-fluorouracil in the palliative treatment of patients with advanced metastatic colorectal cancer.(1)
Limitations of Use
Levoleucovorin injection is not approved for pernicious anemia and megaloblastic anemias. Improper use may cause a hematologic remission while neurologic manifestations continue to progress. (1.1)

2 DOSAGE AND ADMINISTRATION

Do not administer intrathecally. (2.1)

Levoleucovorin injection is dosed at one-half the usual dose of racemic d,l-leucovorin. (2.1)
Levoleucovorin injection Rescue After High-Dose Methotrexate Therapy
Levoleucovorin injection rescue recommendations are based on a methotrexate dose of 12 grams/m^2 administered by intravenous infusion over 4 hours. Levoleucovorin injection rescue at a dose of 7.5 mg (approximately 5 mg/m^2) every 6 hours for 10 doses starts 24 hours after the beginning of the methotrexate infusion. Determine serum creatinine and methotrexate levels at least once daily. Continue Levoleucovorin injection administration, hydration, and urinary alkalinization (pH of 7.0 or greater) until the methotrexate level is below 5 x 10^-8 M (0.05 micromolar). The Levoleucovorin injection dose may need to be adjusted. (2.3)

Levoleucovorin Injection Administration in Combination with 5-Fluorouracil (5-FU)^2^2^2^2

The following regimens have been used historically for the treatment of colorectal cancer:

1. Levoleucovorin injection is administered at 100 mg/m^2 by slow intravenous injection over a minimum of 3 minutes, followed by 5-FU at 370 mg/m^2 by intravenous injection. (2.5)

2. Levoleucovorin injection is administered at 10 mg/m^2 by intravenous injection followed by 5-FU at 425 mg/m^2 by intravenous injection. (2.5)

5-FU and Levoleucovorin injection should be administered separately to avoid the formation of a precipitate.

Treatment is repeated daily for five days. This five-day treatment course may be repeated at 4 week (28-day) intervals, for 2 courses and then repeated at 4 to 5 week (28 to 35 day) intervals provided that the patient has completely recovered from the toxic effects of the prior treatment course.

In subsequent treatment courses, the dosage of 5-FU should be adjusted based on patient tolerance of the prior treatment course. The daily dosage of 5-FU should be reduced by 20% for patients who experienced moderate hematologic or gastrointestinal toxicity in the prior treatment course, and by 30% for patients who experienced severe toxicity. For patients who experienced no toxicity in the prior treatment course, 5-FU dosage may be increased by 10%. Levoleucovorin injection dosages are not adjusted for toxicity. (2.5)

3 DOSAGE FORMS AND STRENGTHS

Levoleucovorin Injection: 17.5 mL of a sterile solution containing levoleucovorin calcium pentahydrate equivalent to 175 mg Levoleucovorin and 0.83% sodium chloride. (3, 11, 16)
Levoleucovorin Injection: 25 mL of a sterile solution containing levoleucovorin calcium pentahydrate equivalent to 250 mg levoleucovorin and 0.83% sodium chloride. (3, 11, 16)

4 CONTRAINDICATIONS

Levoleucovorin is contraindicated for patients who have had previous allergic reactions attributed to folic acid or folinic acid. (4)

5 WARNINGS AND PRECAUTIONS

Due to Ca^++ content, no more than 16 mL (160 mg) of levoleucovorin solution should be injected intravenously per minute. (5.1)
Levoleucovorin injection enhances the toxicity of fluorouracil. (5.2,7) Concomitant use of d,l-leucovorin with trimethoprim sulfamethoxazole for Pneumocystis carinii pneumonia in HIV patients was associated with increased rates of treatment failure in a placebo-controlled study. (5.3)

6 ADVERSE REACTIONS

Allergic reactions were reported in patients receiving Levoleucovorin injection. (6.3)
Vomiting (38%), stomatitis (38%) and nausea (19%) were reported in patients receiving Levoleucovorin injection as rescue after high-dose methotrexate therapy. (6.1)
The most common adverse reactions (>50%) in patients with advanced colorectal cancer receiving Levoleucovorin injection in combination with 5-FU were diarrhea, nausea and stomatitis. (6.2)

To report SUSPECTED ADVERSE REACTIONS, contact Dr.Reddys’ Laboratories Inc., at 1-888-375-3784 or FDA at 1-800-FDA-1088 or

www.fda.gov/medwatch

7 DRUG INTERACTIONS

Levoleucovorin injection may counteract the antiepileptic effect of phenobarbital, phenytoin and primidone, and increase the frequency of seizures in susceptible patients. (7)

FULL PRESCRIBING INFORMATION

1 INDICATIONS AND USAGE

Levoleucovorin injection is a folate analog.

Levoleucovorin injection rescue is indicated after high-dose methotrexate therapy in osteosarcoma.

Levoleucovorin injection is also indicated to diminish the toxicity and counteract the effects of impaired methotrexate elimination and of inadvertent overdosage of folic acid antagonists.

Levoleucovorin injection is indicated for use in combination chemotherapy with 5-fluorouracil in the palliative treatment of patients with advanced metastatic colorectal cancer.

1.1 Limitations of Use

· Levoleucovorin injection is not approved for pernicious anemia and megaloblastic anemias secondary to the lack of vitamin B12.Improper use may cause a hematologic remission while neurologic manifestations continue to progress.

2 DOSAGE AND ADMINISTRATION

2.1 Administration Guidelines

Levoleucovorin injection is dosed at one-half the usual dose of racemic d,l-leucovorin.

Levoleucovorin injection is indicated for intravenous administration only. Do not administer intrathecally.

2.2 Co-administration of Levoleucovorin with other agents

Due to the risk of precipitation, do not co-administer Levoleucovorin injection with other agents in the same admixture.

2.3 Levoleucovorin injection Rescue After High-Dose Methotrexate Therapy

The recommendations for Levoleucovorin injection rescue are based on a methotrexate dose of 12 grams/m^2 administered by intravenous infusion over 4 hours (see methotrexate package insert for full prescribing information). Levoleucovorin injection rescue at a dose of 7.5 mg (approximately 5 mg/m^2) every 6 hours for 10 doses starts 24 hours after the beginning of the methotrexate infusion.

Serum creatinine and methotrexate levels should be determined at least once daily. Levoleucovorin injection administration, hydration, and urinary alkalinization (pH of 7.0 or greater) should be continued until the methotrexate level is below 5 x 10^-8 M (0.05 micromolar). The Levoleucovorin injection dose should be adjusted or rescue extended based on the following guidelines.

Table 1 Guidelines for Levoleucovorin injection Dosage and Administration

Clinical Situation | Laboratory Findings | Levoleucovorin injection Dosage and Duration
Normal Methotrexate Elimination | Serum methotrexate level approximately 10 micromolar at 24 hours after administration, 1 micromolar at 48 hours, and less than 0.2 micromolar at 72 hours | 7.5 mg IV q 6 hours for 60 hours (10 doses starting at 24 hours after start of methotrexate infusion).
Delayed Late Methotrexate Elimination | Serum methotrexate level remaining above 0.2 micromolar at 72 hours, and more than 0.05 micromolar at 96 hours after administration. | Continue 7.5 mg IV q 6 hours, until methotrexate level is less than 0.05 micromolar.
Delayed Early Methotrexate Elimination and/or Evidence of Acute Renal Injury | Serum methotrexate level of 50 micromolar or more at 24 hours, or 5 micromolar or more at 48 hours after administration, OR; a 100% or greater increase in serum creatinine level at 24 hours after methotrexate administration (e.g., an increase from 0.5 mg/dL to a level of 1 mg/dL or more). | 75 mg IV q 3 hours until methotrexate level is less than 1 micromolar; then 7.5 mg IV q 3 hours until methotrexate level is less than 0.05 micromolar.

Patients who experience delayed early methotrexate elimination are likely to develop reversible renal failure. In addition to appropriate levoleucovorin injection therapy, these patients require continuing hydration and urinary alkalinization, and close monitoring of fluid and electrolyte status, until the serum methotrexate level has fallen to below 0.05 micromolar and the renal failure has resolved.

Some patients will have abnormalities in methotrexate elimination or renal function following methotrexate administration, which are significant but less severe than the abnormalities described in the table above. These abnormalities may or may not be associated with significant clinical toxicity. If significant clinical toxicity is observed, Levoleucovorin injection rescue should be extended for an additional 24 hours (total of 14 doses over 84 hours) in subsequent courses of therapy. The possibility that the patient is taking other medications which interact with methotrexate (e.g., medications which may interfere with methotrexate elimination or binding to serum albumin) should always be reconsidered when laboratory abnormalities or clinical toxicities are observed.

Delayed methotrexate excretion may be caused by accumulation in a third space fluid collection (i.e., ascites, pleural effusion), renal insufficiency, or inadequate hydration. Under such circumstances, higher doses of levoleucovorin injection or prolonged administration may be indicated.

Although levoleucovorin injection may ameliorate the hematologic toxicity associated with high-dose methotrexate, levoleucovorin injection has no effect on other established toxicities of methotrexate such as the nephrotoxicity resulting from drug and/or metabolite precipitation in the kidney.

2.4 Dosing Recommendations for Inadvertent Methotrexate Overdosage

Levoleucovorin injection rescue should begin as soon as possible after an inadvertent overdosage and within 24 hours of methotrexate administration when there is delayed excretion. As the time interval between antifolate administration [e.g., methotrexate] and levoleucovorin injection rescue increases, levoleucovorin injection effectiveness in counteracting toxicity may decrease. Levoleucovorin injection 7.5 mg (approximately 5 mg/m^2) should be administered IV every 6 hours until the serum methotrexate level is less than 10^-8 M. Serum creatinine and methotrexate levels should be determined at 24 hour intervals. If the 24 hour serum creatinine has increased 50% over baseline or if the 24 hour methotrexate level is greater than 5 x 10^-6 M or the 48 hour level is greater than 9 x 10^-7 M, the dose of levoleucovorin injection should be increased to 50 mg/m^2 IV every 3 hours until the methotrexate level is less than 10^-8 M. Hydration (3 L/day) and urinary alkalinization with NaHCO3 should be employed concomitantly. The bicarbonate dose should be adjusted to maintain the urine pH at 7.0 or greater.

2.5 Levoleucovorin injection Administration in Combination with 5-Fluorouracil (5-FU)

The following regimens have been used historically for the treatment of colorectal cancer:

1. Levoleucovorin injection is administered at 100 mg/m^2 by slow intravenous injection over a minimum of 3 minutes, followed by 5-FU at 370 mg/m^2 by intravenous injection.

2. Levoleucovorin injection is administered at 10 mg/m^2 by intravenous injection followed by 5-FU at 425 mg/m^2 by intravenous injection. 5-FU and levoleucovorin injection should be administered separately to avoid the formation of a precipitate.

Treatment is repeated daily for five days. This five-day treatment course may be repeated at 4 week (28-day) intervals, for 2 courses and then repeated at 4 to 5 week (28 to 35 day) intervals provided that the patient has completely recovered from the toxic effects of the prior treatment course. In subsequent treatment courses, the dosage of 5-FU should be adjusted based on patient tolerance of the prior treatment course. The daily dosage of 5-FU should be reduced by 20% for patients who experienced moderate hematologic or gastrointestinal toxicity in the prior treatment course, and by 30% for patients who experienced severe toxicity. For patients who experienced no toxicity in the prior treatment course, 5-FU dosage may be increased by 10%. Levoleucovorin injection dosages are not adjusted for toxicity.

2.6 Reconstitution and Infusion Instructions

Levoleucovorin Injection

- Levoleucovorin injection contains no preservative. Observe strict aseptic technique during reconstitution of the drug product.
- Levoleucovorin injection solutions may be further diluted to concentrations of 0.5 mg/mL in 0.9% Sodium Chloride Injection, USP or 5% Dextrose Injection, USP.
- The diluted solution using 0.9% Sodium Chloride Injection, USP or 5% Dextrose Injection, USP may be held at room temperature for not more than 4 hours.
- Visually inspect the diluted solution for particulate matter and discoloration, prior to administration. CAUTION: Parenteral drug products should be inspected visually for particulate matter and discoloration prior to administration, whenever solution and container permit. Do not use if cloudiness or precipitate is observed.
- No more than 16 mL of levoleucovorin Injection (160 mg of levoleucovorin) should be injected intravenously per minute, because of the calcium content of the levoleucovorin solution.

3 DOSAGE FORMS AND STRENGTHS

Levoleucovorin Injection, 175 mg is supplied in a single-dose vial containing 17.5 mL sterile solution. Each mL contains levoleucovorin calcium pentahydrate equivalent to 10 mg levoleucovorin and 8.3 mg sodium chloride.

Levoleucovorin Injection, 250 mg is supplied in a single-dose vial containing 25 mL sterile solution. Each mL contains levoleucovorin calcium pentahydrate equivalent to 10 mg levoleucovorin and 8.3 mg sodium chloride.

4 CONTRAINDICATIONS

Levoleucovorin injection is contraindicated for patients who have had previous allergic reactions attributed to folic acid or folinic acid.

5 WARNINGS AND PRECAUTIONS

5.1 Rate of Administration

Because of the Ca^++ content of the levoleucovorin solution, no more than 16 mL (160 mg of levoleucovorin) should be injected intravenously per minute.

5.2 Potential for Enhanced Toxicity with 5-Fluorouracil

Levoleucovorin injection enhances the toxicity of 5-fluorouracil. Deaths from severe enterocolitis, diarrhea, and dehydration have been reported in elderly patients receiving weekly d,l-leucovorin and 5-fluorouracil. When these drugs are administered concurrently in the palliative treatment of advanced colorectal cancer, the dosage of 5-FU must be lower than usually administered. Although the toxicities observed in patients treated with the combination of levoleucovorin injection and 5-FU are qualitatively similar to those observed with 5-FU alone, gastrointestinal toxicities (particularly stomatitis and diarrhea) are observed more commonly and may be of greater severity and of prolonged duration in patients treated with the combination.

In the first Mayo/NCCTG controlled trial, toxicity, primarily gastrointestinal, resulted in 7% of patients requiring hospitalization when treated with 5-FU alone or 5-FU in combination with 200 mg/m^2 of d,l-leucovorin and 20% when treated with 5-FU in combination with 20 mg/m^2 of d,l-leucovorin. In the second Mayo/NCCTG trial, hospitalizations related to treatment toxicity also appeared to occur more often in patients treated with the low dose d,l-leucovorin/5-FU combination than in patients treated with the high dose combination – 11% versus 3%. Therapy with levoleucovorin injection and 5-FU must not be initiated or continued in patients who have symptoms of gastrointestinal toxicity of any severity, until those symptoms have completely resolved. Patients with diarrhea must be monitored with particular care until the diarrhea has resolved, as rapid clinical deterioration leading to death can occur. In an additional study utilizing higher weekly doses of 5-FU and d,l-leucovorin, elderly and/or debilitated patients were found to be at greater risk for severe gastrointestinal toxicity.

Seizures and/or syncope have been reported rarely in cancer patients receiving d,l-leucovorin, usually in association with fluoropyrimidine administration, and most commonly in those with CNS metastases or other predisposing factors. However, a causal relationship has not been established.

5.3 Potential for interaction with trimethoprim-sulfamethoxazole

The concomitant use of d,l-leucovorin with trimethoprim-sulfamethoxazole for the acute treatment of Pneumocystis carinii pneumonia in patients with HIV infection was associated with increased rates of treatment failure and morbidity in a placebo-controlled study.

6 ADVERSE REACTIONS

6.1 Clinical Studies in High-Dose Methotrexate Therapy

Since clinical trials are conducted under widely varying conditions, adverse reaction rates observed in the clinical trials of a drug cannot be directly compared to rates in the clinical trials of another drug and may not reflect the rates observed in practice. The following table presents the frequency of adverse reactions which occurred during the administration of 58 courses of high-dose methotrexate 12 grams/m^2 followed by Levoleucovorin injection rescue for osteosarcoma in 16 patients age 6 to 21. Most patients received levoleucovorin injection 7.5 mg every 6 hours for 60 hours or longer beginning 24 hours after completion of methotrexate.

Table 2 Adverse Reactions with High-Dose Methotrexate Therapy

Body System/ Adverse Reactions | Number (%) of Patients with Adverse Reactions (N =16) | Number (%) of Courses with Adverse Reactions (N = 58)
All | Grade 3+ | All | Grade 3+
Gastrointestinal
Stomatitis | 6 (37.5) | 1 (6.3) | 10 (17.2) | 1 (1.7)
Vomiting | 6 (37.5) | 0 | 14 (24.1) | 0
Nausea | 3 (18.8) | 0 | 3 (5.2) | 0
Diarrhea | 1 (6.3) | 0 | 1 (1.7) | 0
Dyspepsia | 1 (6.3) | 0 | 1 (1.7) | 0
Typhlitis | 1 (6.3) | 1 (6.3) | 1 (1.7) | 1 (1.7)
Respiratory
Dyspnea | 1 (6.3) | 0 | 1 (1.7) | 0
Skin and Appendages
Dermatitis | 1 (6.3) | 0 | 1 (1.7) | 0
Other
Confusion | 1 (6.3) | 0 | 1 (1.7) | 0
Neuropathy | 1 (6.3) | 0 | 1 (1.7) | 0
Renal function abnormal | 1 (6.3) | 0 | 3 (5.2) | 0
Taste perversion | 1 (6.3) | 0 | 1 (1.7) | 0
Total number of patients | 9 (56.3) | 2 (12.5)
Total number of courses | 25 (43.1) | 2 (3.4)

The incidence of adverse reactions may be underestimated because not all patients were fully evaluable for toxicity for all cycles in the clinical trials. Leukopenia and thrombocytopenia were observed, but could not be attributed to high-dose methotrexate with levoleucovorin injection rescue because patients were receiving other myelosuppressive chemotherapy.

6.2 Clinical Studies in Combination with 5-FU in Colorectal Cancer

A randomized controlled trial conducted by the North Central Cancer Treatment Group (NCCTG) in patients with advanced colorectal cancer failed to show superiority of a regimen of 5-FU + levoleucovorin to 5-FU + d,l-leucovorin in overall survival. Patients were randomized to 5-FU 370 mg/m^2 intravenously and levoleucovorin 100 mg/m^2 intravenously, both daily for 5 days, or with 5-FU 370 mg/m^2 intravenously and d,l-leucovorin 200 mg/m^2 intravenously, both daily for 5 days. Treatment was repeated week 4 and week 8, and then every 5 weeks until disease progression or unacceptable toxicity. The following table presents the most frequent adverse reactions which occurred in patients in the 2 treatment arms.

Table 3 Adverse Reactions Occurring in ≥ 10% of Patients in Either Arm

Adverse Reaction | Levoleucovorin injection /5FU n=318 | d,l-Leucovorin/5FU n=307
Adverse Event N (%) | Grade 1-4 | Grade 3-4 | Grade 1-4 | Grade 3-4
Gastrointestinal
Stomatitis | 229 (72%) | 37 (12%) | 221 (72%) | 44 (14%)
Diarrhea | 222 (70%) | 61 (19%) | 201 (65%) | 51 (17%)
Nausea | 197 (62%) | 25 (8%) | 186 (61%) | 26 (8%)
Vomiting | 128 (40%) | 17 (5%) | 114 (37%) | 18 (6%)
Abdominal Pain^1 | 45 (14%) | 10 (3%) | 57 (19%) | 10 (3%)
General Disorders
Asthenia/Fatigue/Malaise | 91 (29%) | 15 (5%) | 99 (32%) | 34 (11%)
Metabolism and Nutrition
Anorexia/Decreased Appetite | 76 (24%) | 13 (4%) | 77 (25%) | 5 (2%)
Skin Disorders
Dermatitis | 91 (29%) | 3 (1%) | 86 (28%) | 4 (1%)
Alopecia | 83 (26%) | 1 (0.3%) | 87 (28%) | 3 (1%)

^1Includes abdominal pain, upper abdominal pain, lower abdominal pain, and abdominal tenderness

6.3 Postmarketing Experience

Since adverse reactions from spontaneous reports are provided voluntarily from a population of uncertain size, it is not always possible to estimate reliably their frequency or establish a causal relationship to drug exposure. Spontaneously reported adverse reactions collected by the WHO Collaborating Center for International Drug Monitoring in Uppsala Sweden have yielded seven cases where levoleucovorin was administered with a regimen of methotrexate. The events were dyspnea, pruritus, rash, temperature change and rigors. For 217 adverse reactions (108 reports) where levoleucovorin was a suspected or interacting medication, there were 40 occurrences of “possible allergic reactions.”

In an analysis where calcium levoleucovorin injection was reported as the primary suspect drug and fluorouracil (FU) was reported as a concomitant medication, possible allergic reactions were reported among 47 cases (67 events).

7 DRUG INTERACTIONS

Folic acid in large amounts may counteract the antiepileptic effect of phenobarbital, phenytoin and primidone, and increase the frequency of seizures in susceptible children. It is not known whether folinic acid has the same effects.

However, both folic and folinic acids share some common metabolic pathways. Caution should be taken when taking folinic acid in combination with anticonvulsant drugs.

Preliminary human studies have shown that small quantities of systemically administered leucovorin enter the CSF, primarily as its major metabolite, 5-methyltetrahydrofolate (5-MTHFA). In humans, the CSF levels of 5-MTHFA remain 1 to 3 orders of magnitude lower than the usual methotrexate concentrations following intrathecal administration. Levoleucovorin injection increases the toxicity of 5-fluorouracil [see Warnings and Precautions (5.2)].

8 USE IN SPECIFIC POPULATIONS

8.1 Pregnancy

Pregnancy Category C. Animal reproduction studies have not been conducted with levoleucovorin injection. It is not known whether levoleucovorin injection can cause fetal harm when administered to a pregnant woman or can affect reproduction capacity. Levoleucovorin injection should be given to a pregnant woman only if clearly needed.

8.3 Nursing Mothers

It is not known whether this drug is excreted in human milk. Because many drugs are excreted in human milk, and because of the potential for serious adverse reactions in nursing infants from levoleucovorin injection, a decision should be made whether to discontinue nursing or discontinue the drug, taking into account the importance of the drug to the mother.

8.4 Pediatric Use

[See Clinical Studies (14)]

8.5 Geriatric Use

Clinical studies of levoleucovorin injection in the treatment of osteosarcoma did not include subjects aged 65 and over to determine whether they respond differently from younger subjects.

In the NCCTG clinical trial of levoleucovorin injection in combination with 5-FU in advanced colorectal cancer, adverse reactions were consistent with 5-FU related toxicity and were similar for patients age 65 and older and for patients younger than age 65.

10 OVERDOSAGE

No data are available for overdosage with levoleucovorin.

11 DESCRIPTION

Levoleucovorin is the levo isomeric form of racemic d,l-leucovorin, present as the calcium salt. Levoleucovorin is the pharmacologically active isomer of leucovorin [(6-S)-leucovorin].

Levoleucovorin Injection contain levoleucovorin calcium, which is one of several active, chemically reduced derivatives of folic acid. It is useful as antidote to the inhibition of dihydrofolate reductase by methotrexate. This compound has the chemical designation calcium (6S)-N-{4-[[(2-amino-5-formyl-1,4,5,6,7,8-hexahydro-4-oxo-6pteridinyl)methyl] amino]benzoyl}-L-glutamate pentahydrate. The molecular weight is 601.6 and the structural formula is:

Its molecular formula is: C20H21CaN7O7. 5 H2O

Levoleucovorin Injection is supplied as a sterile solution of either 175 mg levoleucovorin in 17.5 mL or 250 mg levoleucovorin in 25 mL. Each mL contains levoleucovorin calcium pentahydrate equivalent to 10 mg levoleucovorin and 8.3 mg sodium chloride. Sodium hydroxide is used for pH adjustment to pH 8.0 (6.5 to 8.5).

12 CLINICAL PHARMACOLOGY

12.1 Mechanism of Action

12.1.1 Levoleucovorin effects during high-dose methotrexate therapy Levoleucovorin is the pharmacologically active isomer of 5-formyl tetrahydrofolic acid. Levoleucovorin does not require reduction by the enzyme dihydrofolate reductase in order to participate in reactions utilizing folates as a source of “onecarbon” moieties. Administration of levoleucovorin can counteract the therapeutic and toxic effects of folic acid antagonists such as methotrexate, which act by inhibiting dihydrofolate reductase.

12.1.2 Levoleucovorin effects in combination with 5-fluorouracil Levoleucovorin can enhance the therapeutic and toxic effects of fluoropyrimidines used in cancer therapy such as 5-fluorouracil. 5-fluorouracil is metabolized to 5-fluoro-2'-deoxyuridine-5'-monophosphate (FdUMP), which binds to and inhibits thymidylate synthase (an enzyme important in DNA repair and replication). Levoleucovorin is readily converted to another reduced folate, 5,10-methylenetetrahydrofolate, which acts to stabilize the binding of FdUMP to thymidylate synthase and thereby enhances the inhibition of this enzyme.

12.2 Pharmacodynamics

Levoleucovorin is actively and passively transported across cell membranes. In vivo, levoleucovorin is converted to 5-methyltetrahydrofolic acid (5-methyl-THF), the primary circulating form of active reduced folate. Levoleucovorin and 5-methyl-THF are polyglutamated intracellularly by the enzyme folylpolyglutamate synthetase. Folylpolyglutamates are active and participate in biochemical pathways that require reduced folate.

12.3 Pharmacokinetics

The pharmacokinetics of levoleucovorin after intravenous administration of a 15 mg dose was studied in healthy male volunteers. After rapid intravenous administration, serum total tetrahydrofolate (total-THF) concentrations reached a mean peak of 1722 ng/mL. Serum (6S)-5-methyl-5,6,7,8-tetrahydrofolate concentrations reached a mean peak of 275 ng/mL and the mean time to peak was 0.9 hours. The mean terminal half-life for total-THF and (6S)-5-methyl-5,6,7,8 tetrahydrofolate was 5.1 and 6.8 hours, respectively.

A pharmacokinetic study was conducted in 40 healthy subjects who received a single intravenous dose of either levoleucovorin (200 mg/m^2) or racemic d,l-leucovorin (400 mg/m^2), each administered as a 2-hour infusion in a crossover design. Results indicate that the 90% confidence interval for the geometric mean ratios for both AUC0-inf and Cmax were within the standard limit of 80 to 125% for both l-leucovorin and l-5-methyl-THF. Therefore, the exposure to l-leucovorin and 5-methyl-THF (AUC0-inf and Cmax) was comparable whether it was administered as levoleucovorin or as d,l-leucovorin. The geometric mean AUC0-inf values for levoleucovorin were 30719 ng.h/mL and 31296 ng.h/mL for levoleucovorin and d,l-leucovorin, respectively. The geometric mean Cmax values for levoleucovorin were 10895 ng/mL and 11301 ng/ mL for levoleucovorin and d,l-leucovorin, respectively. The geometric mean AUC0-inf values for 5-methyl-THF were 52105 ng.h/mL and 50137 ng.h/mL for levoleucovorin and d,l-leucovorin, respectively. The geometric mean Cmax values for 5-methyl-THF were 4930 ng/mL and 4658 ng/mL for levoleucovorin and d,l-leucovorin, respectively.

Use of Levoleucovorin in combination with 5-fluorouracil A published cross study comparison showed that the mean dose-normalized steady-state plasma concentrations for both levoleucovorin and 5-methyl-THF were comparable whether 5-FU (370 mg/m^2/day IV bolus) was given in combination with levoleucovorin (250 mg/m^2 and 1000 mg/m^2 as a continuous IV infusion for 5.5 days, N=9) or in combination with d,l-leucovorin (500 mg/m^2 as a continuous IV infusion for 5.5 days, N=6).

13 NONCLINICAL TOXICOLOGY

13.1 Carcinogenesis, Mutagenesis, Impairment Of Fertility

No studies have been conducted to evaluate the potential of levoleucovorin for carcinogenesis, mutagenesis and impairment of fertility.

13.2 Animal Pharmacology and/or Toxicology

The acute intravenous LD50 values in adult mice and rats were 575 mg/kg (1725 mg/m^2) and 378 mg/kg (2268 mg/m^2), respectively. Signs of sedation, tremors, reduced motor activity, prostration, labored breathing, and/or convulsion were observed in these studies. Anticipated human dose for each administration is approximately 5 mg/m^2 for high-dose methotrexate therapy which represents a 3-log safety margin.

14 CLINICAL STUDIES

14.1 High-Dose Methotrexate Therapy

The safety and efficacy of levoleucovorin rescue following high-dose methotrexate were evaluated in 16 patients age 6 to 21 who received 58 courses of therapy for osteogenic sarcoma. High-dose methotrexate was one component of several different combination chemotherapy regimens evaluated across several trials. Methotrexate 12 g/m^2 IV over 4 hours was administered to 13 patients, who received levoleucovorin 7.5 mg every 6 hours for 60 hours or longer beginning 24 hours after completion of methotrexate. Three patients received methotrexate 12.5 g/m^2 IV over 6 hours, followed by levoleucovorin 7.5 mg every 3 hours for 18 doses beginning 12 hours after completion of methotrexate. The mean number of levoleucovorin doses per course was 18.2 and the mean total dose per course was 350 mg. The efficacy of levoleucovorin rescue following high-dose methotrexate was based on the adverse reaction profile. [See Adverse Reactions (6)]

14.2 Combination with 5-FU in Colorectal Cancer

In a randomized clinical study conducted by the Mayo Clinic and the North Central Cancer Treatment Group (Mayo/NCCTG) in patients with advanced metastatic colorectal cancer, three treatment regimens were compared: d,l-leucovorin (LV) 200 mg/m^2 and 5-fluorouracil (5-FU) 370 mg/m^2 versus LV 20 mg/m^2 and 5-FU 425 mg/m^2 versus 5-FU 500 mg/m^2. All drugs were administered by slow intravenous infusion daily for 5 days repeated every 28 to 35 days. Response rates were 26% (p=0.04 versus 5-FU alone), 43% (p=0.001 versus 5-FU alone) and 10% for the high dose leucovorin, low dose leucovorin and 5-FU alone groups, respectively. Respective median survival times were 12.2 months (p=0.037), 12 months (p=0.050), and 7.7 months. The low dose LV regimen gave a statistically significant improvement in weight gain of more than 5%, relief of symptoms, and improvement in performance status. The high dose LV regimen gave a statistically significant improvement in performance status and trended toward improvement in weight gain and in relief of symptoms but these were not statistically significant.

In a second Mayo/NCCTG randomized clinical study the 5-FU alone arm was replaced by a regimen of sequentially administered methotrexate (MTX), 5-FU, and LV. Response rates with LV 200 mg/m^2 and 5-FU 370 mg/m^2 versus LV 20 mg/m^2 and 5-FU 425 mg/m^2 versus sequential MTX and 5-FU and LV were respectively 31% (p≤0.01), 42% (p≤0.01), and 14%. Respective median survival times were 12.7 months (p≤0.04), 12.7 months (p≤0.01), and 8.4 months. No statistically significant difference in weight gain of more than 5% or in improvement in performance status was seen between the treatment arms.

A randomized controlled trial conducted by the NCCTG in patients with advanced metastatic colorectal cancer failed to show superiority of a regimen of 5-FU + levoleucovorin to 5-FU + d,l-leucovorin in overall survival. Patients were randomized to 5-FU 370 mg/m^2 intravenously and levoleucovorin 100 mg/m^2 intravenously, both daily for 5 days, or with 5-FU 370 mg/m^2 intravenously and d,l-leucovorin 200 mg/m^2 intravenously, both daily for 5 days. Treatment was repeated week 4 and week 8, and then every 5 weeks until disease progression or unacceptable toxicity.

Levoleucovorin is dosed at one-half the usual dose of racemic d,l-leucovorin.

16 HOW SUPPLIED/STORAGE AND HANDLING

Levoleucovorin Injection, 175 mg contains 17.5 mL sterile clear pale yellow color solution in a single-dose vial. Each mL contains levoleucovorin calcium pentahydrate equivalent to 10 mg levoleucovorin and 8.3 mg sodium chloride. 175 mg/17.5 mL solution – NDC 43598-771-11 Levoleucovorin Injection, 250 mg contains 25 mL sterile clear pale yellow color solution in a single-dose vial. Each mL contains levoleucovorin calcium pentahydrate equivalent to 10 mg levoleucovorin and 8.3 mg sodium chloride. 250 mg/25 mL solution – NDC 43598-773-11 Store in refrigerator at 2°C to 8°C (36°F to 46°F). Protect from light. Store in carton until contents are used. Trademarks are the property of their respective owners.

Manufactured by:

Gland Pharma Limited

Pashamylaram,

Hyderabad, INDIA

Distributor:

Dr.Reddy’s Laboratories Inc.,

Princeton, NJ 08540

Issued: 1217

PACKAGE LABEL

Unvarnished Area Consists of: 2D Barcode, Lot Number, Expiry Date and Serial Number